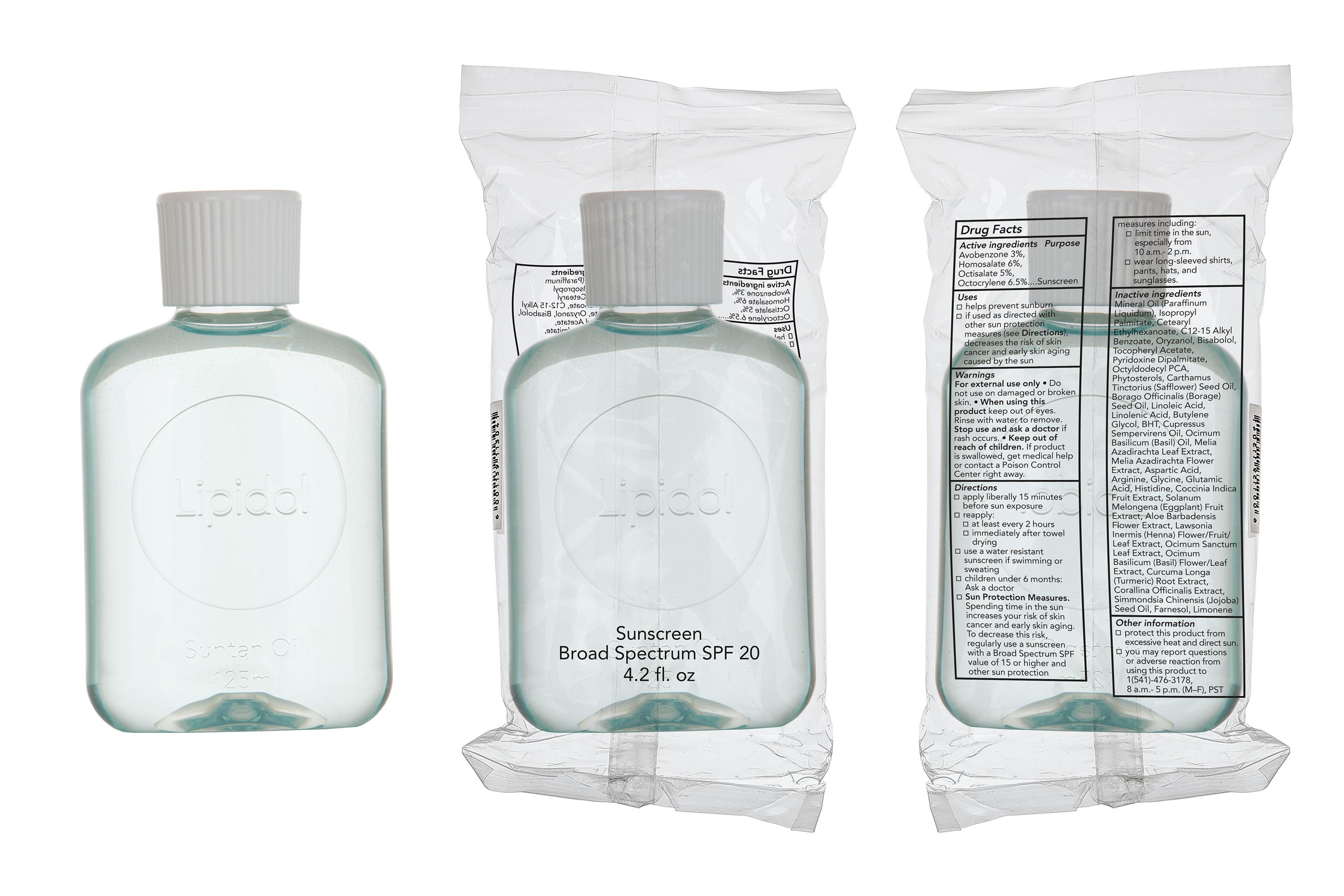 DRUG LABEL: Lipidol
NDC: 69359-000 | Form: OIL
Manufacturer: UNION-SWISS (PTY) LTD
Category: otc | Type: HUMAN OTC DRUG LABEL
Date: 20151124

ACTIVE INGREDIENTS: AVOBENZONE 3 g/100 mL; HOMOSALATE 6 g/100 mL; OCTISALATE 5 g/100 mL; OCTOCRYLENE 6.5 g/100 mL
INACTIVE INGREDIENTS: MINERAL OIL; ISOPROPYL PALMITATE; CETEARYL ETHYLHEXANOATE; C12-15 ALKYL BENZOATE; GAMMA ORYZANOL; LEVOMENOL; .ALPHA.-TOCOPHEROL ACETATE; PYRIDOXINE DIPALMITATE; CERAMIDE 1; .BETA.-SITOSTEROL; SAFFLOWER SEED; BORAGO OFFICINALIS SEED; LINOLEIC ACID; LINOLENIC ACID; BUTYLENE GLYCOL; BUTYLATED HYDROXYTOLUENE; CUPRESSUS SEMPERVIRENS LEAF OIL; OCIMUM BASILICUM WHOLE; AZADIRACHTA INDICA WHOLE; ASPARTIC ACID; ARGININE; GLYCINE; GLUTAMIC ACID; HISTIDINE; COCCINIA GRANDIS FRUIT; SOLANUM MELONGENA WHOLE; ALOE VERA FLOWER; LAWSONIA INERMIS WHOLE; OCIMUM TENUIFLORUM WHOLE; CURCUMA LONGA WHOLE; CORALLINA OFFICINALIS; JOJOBA OIL; FARNESOL; LIMONENE, (+)-

Active Ingredients Purpose

Avobenzone 3%

Homosalate 6%

Octisalate 5%

Octocrylene 6.5% ............................... Sunscreen

Uses

- helps prevent sunburn
- if used as directed with other sun protection measures (see Directions), decreases the risk of skin cancer and early skin aging caused by the sun

Keep out of reach of children. If product is swallowed, get medical help or contact a Poison Control Center right away.

INDICATIONS AND USAGE

Lipidol

Sunscreen Broad Spectrum SPF 20

4.2 fl. oz.

Directions
apply liberally 15 minutes before sun exposure
reapply:

- at least every 2 hours
- immediately after towel drying

use a water resistant sunscreen if swimming or sweating
children under 6 months: Ask a doctor
Sun Protection Measures. Spending time in the sun increases your risk of skin cancer and early skin aging. To decrease this risk, regularly use a sunscreen with a Broad Spectrum SPF value of 15 or higher and other sun protection measures including:

- limit time in the sun, especially from 10 a.m.-2p.m.
- wear long-sleeved shirts, pants, hats, and sunglasses

Warnings

For external use only

Do not use on damaged or broken skin.

When using this product keep out of eyes. Rinse with water to remove.

Stop use and ask a doctor if rash occurs.

Inactive Ingredients

mineral oil (paraffinum liquidum), isopropyl palmitate, cetearyl ethylhexanoate, C12-15 alkyl benzoate, oryxanol, bisabolol, tocopheryl acetate, pyridoxine dipalmitate, octyldodecyl PCA, phytosterols, carthamus tinctorius (safflower) seed oil, borago officinalis (borage) seed oil, linoleic acid, linolenic acid, butylene glycol, BHT, cupressus simpervirens oil, ocimum basilicum (basil) oil, melia azadirachta leaf extract, melia azadirachta flower extract, aspartic acid, arginine, glycine, glutamic acid, histidine, coccinia indica fruit extract, solanum melongena (eggplant) fruit extract, aloe barbadensis flower extract, lawsonia inermis (henna) flower/fruit/leaf extract, ocimum sanctum leaf extract, ocimum basilicum (basil) flower/leaf extract, curcuma longa (turmeric) root extract, corallina officinalis extract, simmondsia chinensis (jojoba) seed oil, farnesol, limonene